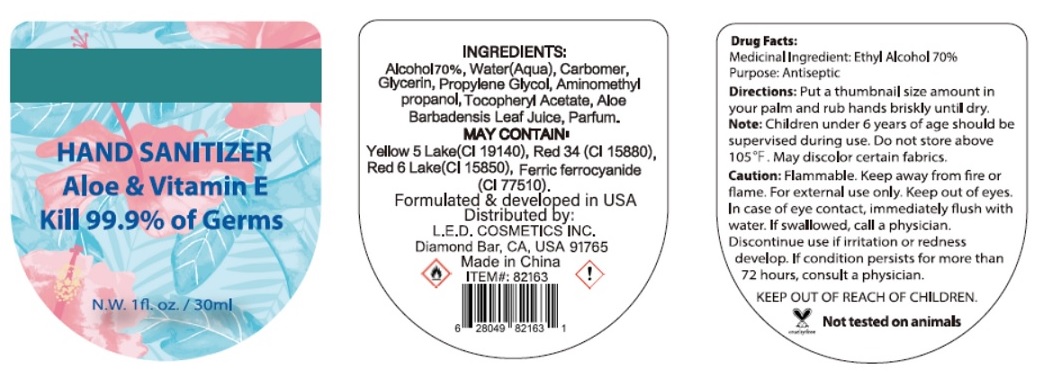 DRUG LABEL: Hand Sanitizer
NDC: 77725-002 | Form: LIQUID
Manufacturer: L.E.D. Cosmetics, Inc.
Category: otc | Type: HUMAN OTC DRUG LABEL
Date: 20200526

ACTIVE INGREDIENTS: ALCOHOL 70 mL/100 mL
INACTIVE INGREDIENTS: WATER; CARBOMER HOMOPOLYMER, UNSPECIFIED TYPE; GLYCERIN; PROPYLENE GLYCOL; .ALPHA.-TOCOPHEROL ACETATE; AMINOMETHYLPROPANOL; ALOE VERA LEAF; FD&C YELLOW NO. 5; D&C RED NO. 34; D&C RED NO. 6 BARIUM LAKE; FERRIC FERROCYANIDE

Hand Sanitizer

Medicinal Ingredient: Ethyl Alcohol 70%

Purpose: Antiseptic

Directions:

Put a thumbnail size amount in your palm and rub hands briskly until dry.

Note:

Children under 6 years of age should be supervised during use.

STORAGE AND HANDLING

Do not store above 105°C. May discolor certain fabrics.

Caution:

Flammable. Keep away from fire or flame. For external use only. Keep out of eyes. In case of eye contact, immediately flush with water. If swallowed, call a physician. Discontinue use if irritation or redness develop. If condition persists for more than 72 hours, consult a physician.

KEEP OUT OF REACH OF CHILDREN.

INGREDIENTS:

Alcohol (70%), Water(Aqua), Carbomer, Glycerin, Propylene Glycol, Aminomethyl Propanol, Tocopheryl Acetate, Aloe Barbadensis Leaf Juice, Parfum.

MAY CONTAIN.

Yellow 5 Lake(CI 19140), Red 34 (CI 15880), Red 6 Lake(CI 15850), Ferric Ferrocyanide (CI 77510).

Aloe & Vitamin E

Kill 99.9% of Germs

Formulated & developed in USA

Distributed by:

L.E.D COSMETICS INC.

Diamond Bar, CA, USA. 91765

Made in China

cruelty free Not tested on animals